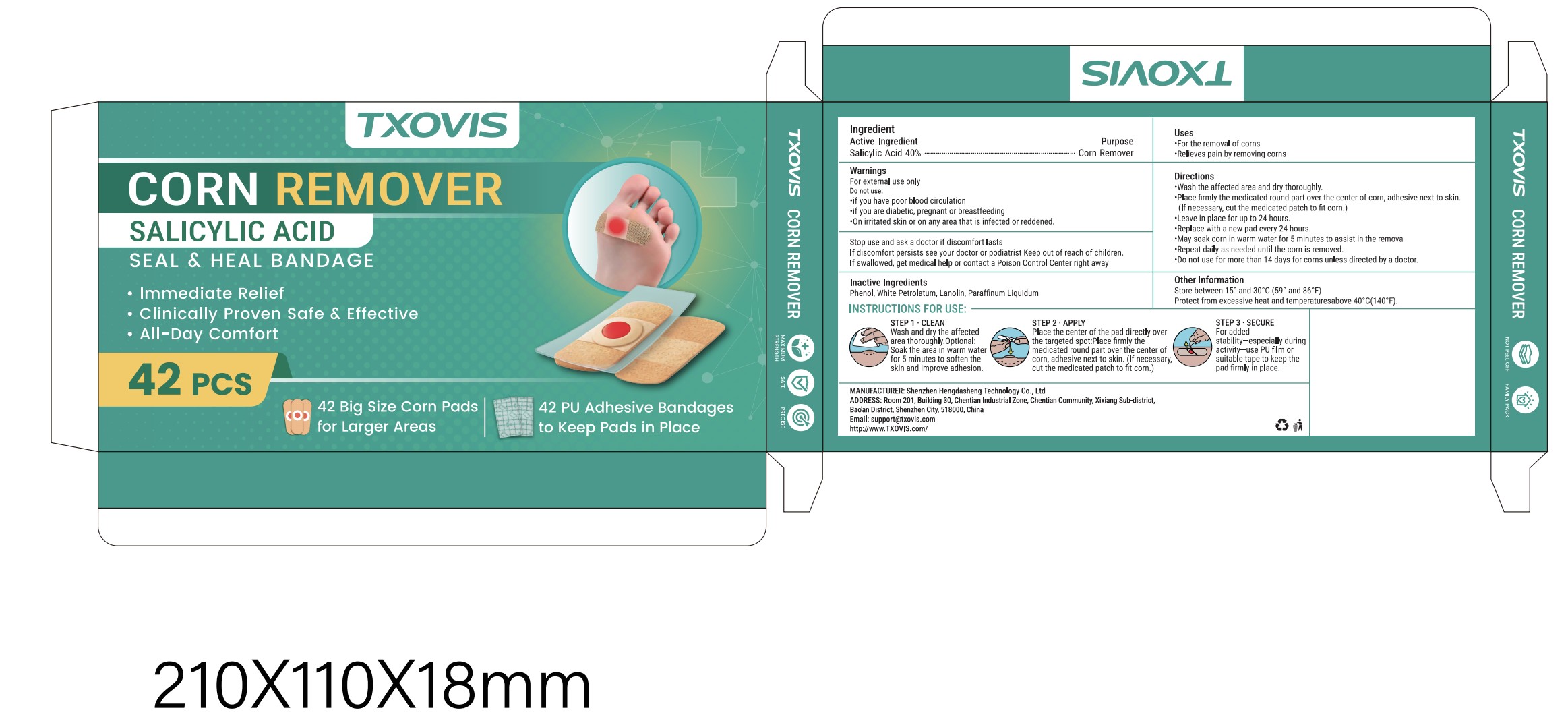 DRUG LABEL: CORN REMOVER
NDC: 87308-002 | Form: PATCH
Manufacturer: Shenzhen Hengdasheng Technology Co., Ltd
Category: otc | Type: HUMAN OTC DRUG LABEL
Date: 20260117

ACTIVE INGREDIENTS: SALICYLIC ACID 40 U/100 U
INACTIVE INGREDIENTS: PHENOL; WHITE PETROLATUM; LANOLIN; PARAFFINUM LIQUIDUM

87308-002
CORN REMOVER

Active Ingredient(s)

Salicylic Acid 40%

Purpose

Corn Remover

Use

For the removal of corns

Relieves pain by removing corns

Warnings

For external use only

Do not use

if you have poor blood circulation

if you are diabetic, pregnant or breastfeeding

On irritated skin or on any area that is infected or reddened.

Do not use with other topical products on the same area unless directed by a doctor.

Stop use and ask a doctor if discomfort lasts

If discomfort persists see your doctor or podiatrist Keep out of reach of children.

If swallowed,get medical help or contact a Poison Control Center right away

Please keep out of reach of children

Directions

1. Wash the affected area and dry thoroughly.

2. Place firmly the medicated round part over the center of corn, adhesive next to skin.(If necessary, cut the medicated patch to fit corn.)

3. Leave in place for up to24 hours.

4. Replace with a new pad every24 hours.

5. May soak corn in warm water for 5 minutes to assist in the remova.

6. Repeat daily as needed until the corn is removed.

7. Do not use for more than 14 days for corns unless directed by a doctor.

Other information

Store between 15° and 30°C(59° and 86°F)

Protect from excessive heat and temperaturesabove 40°C(140°F).

Inactive ingredients

Phenol, White Petrolatum, Lanolin, Paraffinum Liquidum